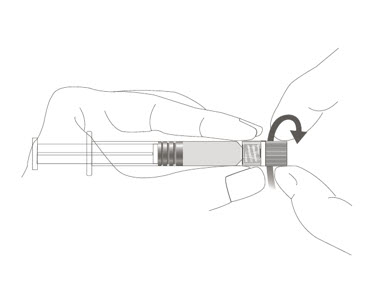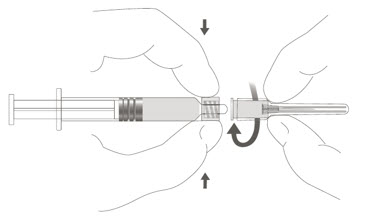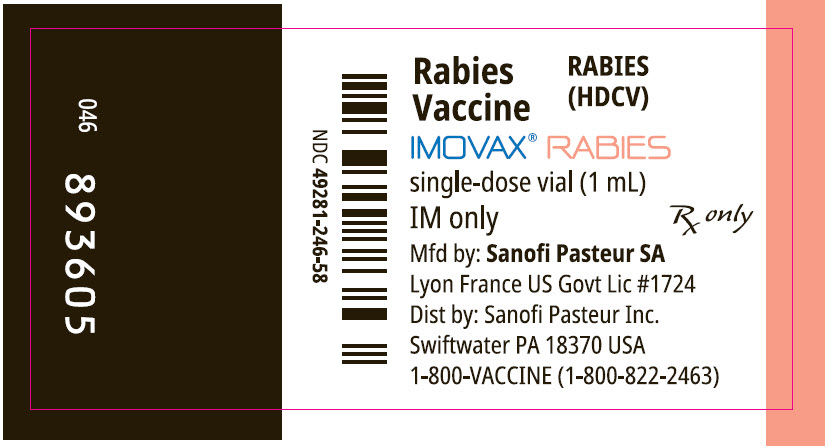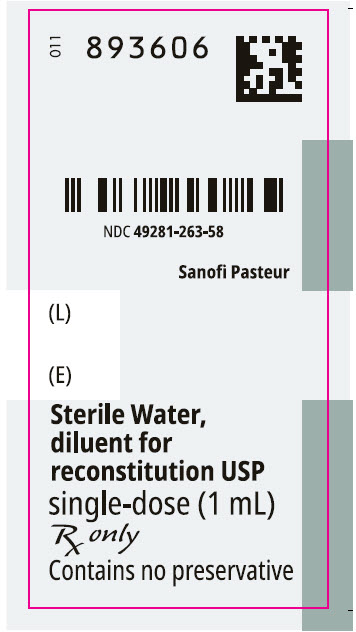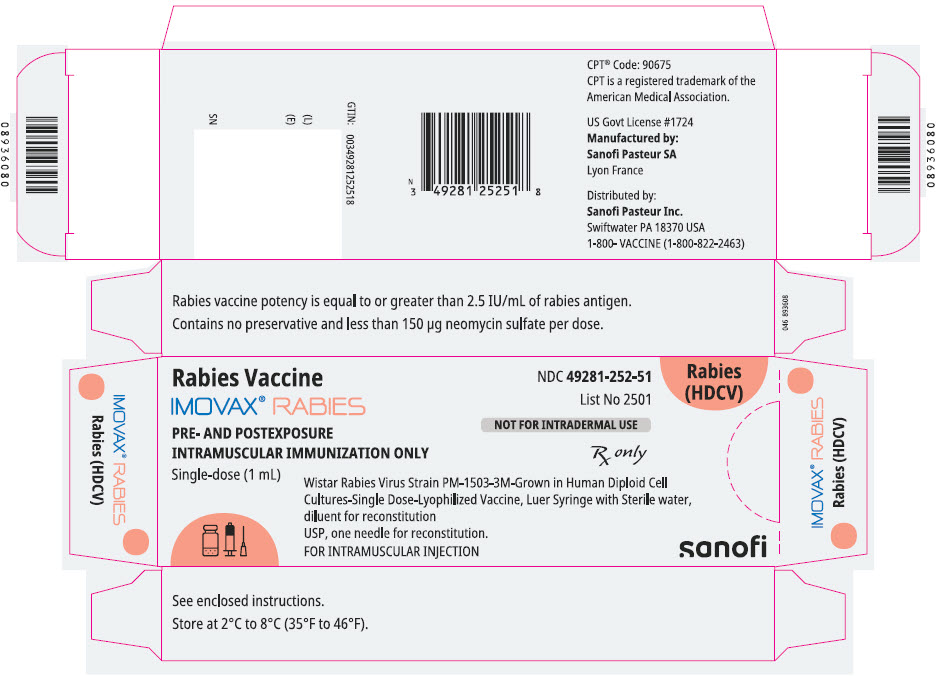 DRUG LABEL: IMOVAX RABIES
NDC: 49281-252 | Form: KIT | Route: INTRAMUSCULAR
Manufacturer: Sanofi Vaccines US Inc.
Category: other | Type: VACCINE LABEL
Date: 20260202

ACTIVE INGREDIENTS: RABIES VIRUS STRAIN PM-1503-3M ANTIGEN (PROPIOLACTONE INACTIVATED) 2.5 [iU]/1 mL
INACTIVE INGREDIENTS: ALBUMIN HUMAN 100 mg/1 mL; NEOMYCIN SULFATE 150 ug/1 mL; PHENOLSULFONPHTHALEIN 20 ug/1 mL; WATER

HIGHLIGHTS OF PRESCRIBING INFORMATION

These highlights do not include all the information needed to use IMOVAX® RABIES safely and effectively. See full prescribing information for IMOVAX® RABIES.
IMOVAX® RABIES (Rabies Vaccine) for injectable suspension, for intramuscular use
Initial U.S. Approval: 1980

RECENT MAJOR CHANGES

Dosage and Administration, Pre-exposure Prophylaxis Dose and Schedule (2.1) | 7/2025

1 INDICATIONS AND USAGE

IMOVAX RABIES is a vaccine indicated for the prevention of rabies in all age groups. IMOVAX RABIES is approved for pre-exposure prophylaxis and post-exposure prophylaxis to prevent rabies. (1)

2 DOSAGE AND ADMINISTRATION

For intramuscular use. Each dose of IMOVAX RABIES is 1 mL. The vaccination schedule differs depending on whether IMOVAX RABIES is administered for pre-exposure prophylaxis or post-exposure prophylaxis. (2.1, 2.2)

3 DOSAGE FORMS AND STRENGTHS

For injectable suspension. (3) Supplied as lyophilized vaccine in a single-dose vial which must be reconstituted with Sterile Water diluent in the accompanying prefilled syringe to form IMOVAX RABIES. (11)

4 CONTRAINDICATIONS

- Pre-exposure prophylaxis: known life-threatening systemic hypersensitivity reaction to any component of the vaccine. (4)
- Post-exposure prophylaxis: no contraindication. (4)

5 WARNINGS AND PRECAUTIONS

- Individuals with altered immunocompetence may have reduced immune response to IMOVAX RABIES. (5.1)
- In individuals who have experienced an anaphylactic reaction following a dose of IMOVAX RABIES, the risk of developing rabies must be carefully considered in decisions regarding the discontinuation of post-exposure vaccination. (5.2)
- Do not inject the vaccine into the gluteal area. (5.4)
- Do not inject the vaccine intradermally. (5.4)

6 ADVERSE REACTIONS

The most commonly reported adverse reactions were:

- Five-dose regimen for post-exposure prophylaxis: the commonly reported local adverse reactions (≥25%) were pain, erythema, swelling, and itching; the commonly reported systemic adverse reactions (≥20%) were headache, nausea, abdominal pain, muscle aches, and dizziness.
- Three-dose regimen for pre-exposure prophylaxis: the most commonly reported solicited adverse reactions (≥10%) were injection site pain (30.4% and 43.5%), headache (27.5% and 19.6%), malaise (23.2% and 17.4%) and myalgia (18.8% and 10.9%) (in participants 18 years of age and older and participants 2 years through 17 years of age, respectively); and fever (17.4%) (in participants 2 years through 17 years of age).
- Two-dose regimen for pre-exposure prophylaxis: the most commonly reported solicited adverse reactions (≥10%) were injection site pain (35.4% and 25.7%) and headache (21.3% and 13.9%) (in participants 18 years of age and older and participants 2 years through 17 years of age, respectively); malaise (26.0%) and myalgia (22.8%) (in participants 18 years of age and older). (6.1)

To report SUSPECTED ADVERSE REACTIONS, contact Sanofi Pasteur Inc. at 1-800-822-2463 (1-800-VACCINE) or VAERS at 1-800-822-7967 and http://vaers.hhs.gov.

7 DRUG INTERACTIONS

Immunosuppressive agents should not be administered during post-exposure prophylaxis unless essential for the treatment of other conditions. (7.1)

FULL PRESCRIBING INFORMATION

1 INDICATIONS AND USAGE

IMOVAX RABIES is a vaccine indicated for the prevention of rabies in all age groups.

- IMOVAX RABIES is approved for pre-exposure prophylaxis to prevent rabies.
- IMOVAX RABIES is approved for post-exposure prophylaxis to prevent rabies.

2 DOSAGE AND ADMINISTRATION

For intramuscular use

2.1 Pre-exposure Prophylaxis Dose and Schedule

Each dose of IMOVAX RABIES is 1 mL.

Primary Vaccination series:

- Three-dose schedule: Administer a dose at Day 0, 7, and 21 or 28
  OR
- Two-dose schedule: Administer a dose at Day 0 and 7

Booster:

Administer a single dose of IMOVAX RABIES.

The United States Centers for Disease Control and Prevention (CDC) has published clinical guidance on administration of booster doses of rabies vaccine depending on rabies exposure risk and for vaccination of individuals who are immunocompromised or who are receiving chloroquine or drugs related to chloroquine. (1) [see Warnings and Precautions (5.1) and Drug Interactions (7.1)]

2.2 Post-exposure Prophylaxis Dose and Schedule

Each dose of IMOVAX RABIES is 1 mL.

The IMOVAX RABIES post-exposure prophylaxis schedule depends on whether or not the individual has been previously vaccinated and/or immunized against rabies. The CDC considers individuals to be previously vaccinated if they received one of the recommended cell-culture vaccines either in a pre-exposure or post-exposure prophylaxis regimen, or they received another vaccine regimen (or vaccines other than cell-culture vaccine) and had a documented adequate rabies virus neutralizing antibody (RVNA) response (defined as ≥ 0.5 IU/mL by Rapid Fluorescent Focus Inhibition Test [RFFIT]). (2)

Previously Vaccinated Individuals

In previously vaccinated individuals (see definition above),

- Administer a dose of IMOVAX RABIES immediately after exposure (at Day 0) and at Day 3.

Unvaccinated or Immunosuppressed (irrespective of previous vaccination status) Individuals

For individuals who have not previously received rabies vaccine, or who are immunosuppressed,

- Administer a dose of IMOVAX RABIES immediately after exposure (at Day 0) and at Day 3, 7, 14, and 28. Administer each dose of IMOVAX RABIES at an anatomical site distant from the Human Rabies Immunoglobulin (HRIG) administration site(s).
- Administer HRIG at Day 0 according to its Prescribing Information.
- Post-vaccination serologic testing is indicated when the individual is known to be immunosuppressed. (3) Contact local or state health department or CDC for recommendations for serologic testing. (3)

Individuals with Uncertain Immune Status

In individuals whose RVNA status is not known and who 1) have not received the full recommended regimen of a cell culture vaccine either in a pre-exposure or post-exposure prophylaxis regimen OR 2) received another (non-cell culture) rabies vaccine regimen,

- Administer a dose of IMOVAX RABIES immediately after exposure (at Day 0) and at Day 3, 7, 14, and 28. Administer each dose of IMOVAX RABIES at an anatomical site distant from the HRIG administration site(s).
- Administer HRIG at Day 0 according to its Prescribing Information.
- If antibody levels ≥ 0.5 IU/mL by RFFIT can be demonstrated in a serum sample collected before vaccine is given, vaccinations may be discontinued after at least two doses of IMOVAX RABIES. (1) (2)

2.3 Preparation

IMOVAX RABIES is supplied in a package containing a vial of lyophilized vaccine, a Luer-Lok prefilled syringe containing 1 mL of Sterile Water diluent with a plunger rod either inserted into the syringe or provided separately, and a sterile reconstitution needle. Reconstitute the lyophilized vaccine with the Sterile Water diluent to form IMOVAX RABIES, as described in the instructions below.

Instructions for vaccine reconstitution

Step 1: Screw the plunger rod into the syringe containing Sterile Water diluent if the plunger rod is provided separately.

Step 2: Hold the syringe cap (avoid holding the plunger rod or syringe barrel) and unscrew the tip cap by twisting it counterclockwise.

Step 3: Attach the reconstitution needle to the syringe, by gently twisting the needle clockwise into the syringe until slight resistance is felt.

Step 4: Transfer the entire content of the syringe containing Sterile Water diluent into the vial containing lyophilized vaccine.

Step 5: Gently swirl the vial until completely dissolved. After reconstitution, IMOVAX RABIES is pink to red.

Step 6: Unscrew the syringe from the reconstitution needle to eliminate negative pressure.
Reattach the syringe to the reconstitution needle which has remained in the vial.

Step 7: Withdraw the total content of the vial (approximately 1 mL) containing reconstituted vaccine. Remove the reconstitution needle and discard it.

Step 8: Attach a new sterile needle (as per Step 3) of a proper length and gauge suitable for intramuscular administration.

Parenteral drug products should be inspected for particulate matter and discoloration prior to administration, whenever solution and container permit. If either of these conditions exist, IMOVAX RABIES should not be administered.

2.4 Administration

Administer IMOVAX RABIES intramuscularly immediately after reconstitution.

For adults and older children, the vaccine should be injected into the deltoid muscle. (4) (5) (6) In infants and small children, the anterolateral aspect of the thigh may be preferable, depending on age and body mass.

Do not administer in the gluteal area [see Warnings and Precautions (5.4)].

Do not administer intradermally [see Warnings and Precautions (5.4)].

3 DOSAGE FORMS AND STRENGTHS

For injectable suspension. A single dose after reconstitution is 1 mL.

4 CONTRAINDICATIONS

Pre-exposure Prophylaxis

Do not administer to anyone with a known life-threatening systemic hypersensitivity reaction to any component of the vaccine [See Warnings and Precautions (5.2) and Description (11)].

Post-exposure Prophylaxis

None.

5 WARNINGS AND PRECAUTIONS

5.1 Altered Immunocompetence

Individuals with altered immunocompetence, including those receiving immunosuppressant therapy, may have reduced immune response to IMOVAX RABIES [See Dosage and Administration (2.1, 2.2) and Drug Interactions (7.1)].

5.2 Management of Allergic Reactions

Appropriate medical treatment must be immediately available to manage potential anaphylactic reactions following administration of IMOVAX RABIES.

In individuals who have experienced an anaphylactic reaction following a dose of IMOVAX RABIES, the risk of developing rabies must be carefully considered in decisions regarding the discontinuation of post-exposure prophylaxis vaccination.

5.3 Other Adverse Reactions

- Once initiated, rabies prophylaxis should not be interrupted or discontinued because of local or mild systemic adverse reactions to rabies vaccine [See Adverse Reactions (6)].
- Serious neuroparalytic reactions occurring during the administration of rabies vaccines pose a dilemma for the attending physician. An individual's risk of developing rabies must be carefully considered before deciding to discontinue vaccination. Moreover, the use of corticosteroids to treat life-threatening neuroparalytic reactions carries the risk of inhibiting the development of active immunity to rabies. It is especially important in these cases that the serum of the patient be tested for RVNA titers. Advice and assistance on the management of serious adverse reactions in individuals receiving rabies vaccines may be sought from the local or state health department. (7)
- Individuals who have experienced "immune complex-like" hypersensitivity reactions should receive no further doses of IMOVAX RABIES unless they are exposed to rabies or they are truly likely to be inapparently and/or unavoidably exposed to rabies virus and have unsatifactory RVNA titers.

5.4 Administration Precautions

- Do not inject the vaccine into the gluteal area as administration in this area may result in lower RVNA titers. (3) There have been reports of possible vaccine failure when the vaccine has been administered in this area. Presumably, subcutaneous fat in the gluteal area may interfere with the immune response to IMOVAX RABIES. (4) (8)
- Do not inject the vaccine intradermally.
- The product is provided in a single-dose vial. Because the single-dose vial contains no preservative, it is not to be used as a multi-dose vial for intradermal injection. In both pre-exposure and post-exposure immunization, the full 1 mL dose should be given intramuscularly.

5.5 Serum Sickness Type Reactions

Serum sickness type reactions have been reported in individuals receiving booster doses of rabies vaccine for pre-exposure prophylaxis. The reaction is characterized by onset approximately 2 to 21 days post-booster, presents with a generalized urticaria, and may also include arthralgia, arthritis, angioedema, nausea, vomiting, fever, and malaise. None of the reported reactions were life-threatening. This has been reported in up to 7% of individuals receiving booster vaccination. (9)

5.6 Guillain-Barré Syndrome

Rare cases of neurologic illness resembling Guillain-Barré syndrome, (10) (11) a transient neuroparalytic illness, that resolved without sequelae in 12 weeks and a focal subacute central nervous system disorder temporally associated with IMOVAX RABIES, have been reported. (12)

5.7 Creutzfeldt-Jakob Disease

This product contains albumin, a derivative of human blood. Based on effective donor screening and product manufacturing processes, it carries an extremely remote risk for transmission of viral diseases and variant Creutzfeldt-Jakob disease (vCJD). There is a theoretical risk for transmission of Creutzfeldt-Jakob disease (CJD), but if that risk actually exists, the risk of transmission would also be considered extremely remote. No cases of transmission of viral diseases, CJD, or vCJD have ever been identified for licensed albumin or albumin contained in other licensed products.

5.8 Limitations of Vaccine Effectiveness

Vaccination with IMOVAX RABIES may not protect all individuals.

5.9 Syncope

Syncope (fainting) has been reported following vaccination with IMOVAX RABIES. Procedures should be in place to avoid injury from fainting.

6 ADVERSE REACTIONS

In a clinical trial evaluating a five-dose regimen for post-exposure prophylaxis, the commonly reported local adverse reactions (≥25%) were pain, erythema, swelling, and itching; the commonly reported systemic adverse reactions (≥20%) were headache, nausea, abdominal pain, muscle aches, and dizziness.

In a clinical trial evaluating the three-dose regimen for pre-exposure prophylaxis, the most commonly reported adverse reactions (≥10%) were injection site pain (30.4% and 43.5%), headache (27.5% and 19.6%), malaise (23.2% and 17.4%) and myalgia (18.8% and 10.9%) (percentages reflect rates in participants 18 years of age and older and participants 2 years through 17 years of age, respectively), fever (17.4%) (in participants 2 years through 17 years of age).

In a clinical trial evaluating the two-dose regimen for pre-exposure prophylaxis, the most commonly reported adverse reactions (≥10%) were injection site pain (35.4% and 25.7%) and headache (21.3% and 13.9%) (percentages reflect rates in participants 18 years of age and older and participants 2 years through 17 years of age, respectively), malaise (26.0%) and myalgia (22.8%) (in participants 18 years of age and older).

6.1 Clinical Trials Experience

Because clinical trials are conducted under widely varying conditions, adverse reaction rates observed in the clinical trials of a vaccine cannot be directly compared with rates in the clinical trials of another vaccine and may not reflect the rates observed in practice.

Post-exposure Prophylaxis

Reactions after vaccination with IMOVAX RABIES have been observed. (9) In a study using five doses of IMOVAX RABIES, local reactions such as pain, erythema, swelling or itching at the injection site were reported in about 25% of recipients of IMOVAX RABIES, and mild systemic reactions such as headache, nausea, abdominal pain, muscle aches, and dizziness were reported in about 20% of recipients. (7)

Pre-exposure Prophylaxis

The 2-dose and 3-dose pre-exposure prophylaxis regimens of IMOVAX RABIES were evaluated in two clinical trials.

Study 1 (NCT03700242), a randomized, open-label, controlled multicenter study included healthy participants 2 years of age and older. In this study, the safety analysis set included 228 participants who received a 2-dose pre-exposure prophylaxis regimen (on Day 0 and Day 7) and 115 participants who received a 3-dose pre-exposure prophylaxis regimen (on Day 0, Day 7 and Day 21). Of these participants, 101 were 2 years through 11 years of age (66 received 2-dose regimen, 35 received 3-dose regimen), 46 were 12 years through 17 years of age (35 received 2-dose regimen, 11 received 3-dose regimen), and 196 were 18 years through 59 years of age (127 received 2-dose regimen, 69 received 3-dose regimen).

Study 2 (NCT04127786), an observer blind, randomized, controlled multicenter study included healthy participants 1 year of age and older. In this study, the safety analysis set included 139 participants who received a 2-dose pre-exposure prophylaxis regimen (on Day 0, and Day 7) and 200 participants who received a 3-dose pre-exposure prophylaxis regimen (on Day 0, Day 7, and Day 28). Of those who received the 3-dose pre-exposure prophylaxis regimen, 100 participants were 1 year through 17 years of age (70 from 1 year through 11 years of age and 30 from 12 years through 17 years of age) and 100 participants were 18 years of age and older, including 2 participants 65 years of age and older. Per study design, no participants 1 year through 17 years of age were included in the 2-dose pre-exposure prophylaxis regimen group.

In both Study 1 and 2, solicited local (injection site) and systemic adverse reactions were recorded by participants or by parents/guardians in a diary card daily for 7 days after any dose. At subsequent visits, approximately 7 to 21 days post-vaccination, participants or parents/guardians reviewed diary cards with study investigators and when necessary, made corrections or clarifications. Unsolicited non-serious adverse events were recorded through 28 days after any dose, and serious adverse events were recorded for at least 6 months following the last vaccination.

The solicited adverse reactions that occurred within 7 days following any dose of IMOVAX RABIES in participants 18 years and older and participants 2 years through 17 years of age in Study 1 are presented in Table 1.

Table 1: Percentages of Participants with Solicited Local and Systemic Adverse Reactions within 7 Days after 2-dose and 3-dose Pre-exposure Prophylaxis Regimens of IMOVAX RABIES (Study 1)
 | ≥ 18 years of age |  | 2 years through 17 years of age
Solicited Adverse Reactions | IMOVAX RABIES 2-dose Pre-exposure Prophylaxis (N=127) | IMOVAX RABIES 3-dose Pre-exposure Prophylaxis (N=69) | IMOVAX RABIES 2-dose Pre-exposure Prophylaxis (N=101) | IMOVAX RABIES 3-dose Pre-exposure prophylaxis (N=46)
Local (injection site)
Pain, any [Any: From "easily tolerated" to "unable to perform usual activities" (2 years through 11 years of age) or from "no interference" to "significant interference with daily activities" (> 12 years); Grade 3: Unable to perform usual activities (2 years through 11 years of age) and prevents daily activity (>12 years)] | 35.4 | 30.4 | 25.7 | 43.5
Pain, Grade 3 | 0.0 | 0.0 | 0.0 | 0.0
Erythema, any [Any: 0 mm (2 years through 11 years of age) and ≥ 25 mm (>12 years); Grade 3: 50 mm (2 years through 11 years) and > 100 mm (>12 years)] | 0.0 | 2.9 | 1.0 | 2.2
Erythema, Grade 3 | 0.0 | 0.0 | 0.0 | 0.0
Swelling, any | 0.0 | 1.4 | 2.0 | 6.5
Swelling, Grade 3 | 0.0 | 0.0 | 0.0 | 0.0
Systemic
Fever, any [Any: ≥ 100.4°F (38.0°C); Grade 3: ≥ 102.1°F (39.0°C)] | 4.7 | 7.2 | 4.0 | 17.4
Fever, Grade 3 | 0.8 | 1.4 | 2.0 | 2.2
Headache, any [Any: From "no interference" to "significant interference with daily activities"; Grade 3: Prevents daily activity] | 21.3 | 27.5 | 13.9 | 19.6
Headache, Grade 3 | 0.0 | 0.0 | 0.0 | 0.0
Malaise, any | 26.0 | 23.2 | 9.9 | 17.4
Malaise, Grade 3 | 0.8 | 0.0 | 0.0 | 0.0
Myalgia, any | 22.8 | 18.8 | 5.9 | 10.9
Myalgia, Grade 3 | 0.0 | 0.0 | 0.0 | 0.0
N = Number of participants who received at least one dose

In Study 2 participants, the commonly reported adverse reactions were generally consistent with those reported in Study 1 participants. In the two participants 1 year to less than 2 years of age in Study 2, the only reported systemic adverse reactions were vomiting and abnormal crying, both occurring in the same participant.

In both Study 1 and Study 2, most solicited adverse reactions resolved within 3 days. No related serious adverse events or deaths were reported in either study.

6.2 Postmarketing Experience

The following additional adverse events have been identified during postmarketing use of IMOVAX RABIES. Because these reactions are reported voluntarily from a population of uncertain size, it is not always possible to reliably estimate their frequency or establish a causal relationship to IMOVAX RABIES exposure.

Blood and Lymphatic System Disorders

Lymphadenopathy

Immune System Disorders

Anaphylactic reaction, serum sickness type reaction, dermatitis allergic, pruritus (itching), edema

Nervous System Disorders

Paresthesia, neuropathy, convulsion, encephalitis, syncope

Gastrointestinal Disorders

Vomiting, diarrhea

Musculoskeletal and Connective Tissue Disorders

Arthralgia

General Disorders and Administration Site Conditions

Asthenia, malaise, fever and chills (shivering), injection site hematoma

Respiratory, Thoracic, and Mediastinal Disorders

Wheezing, dyspnea

7 DRUG INTERACTIONS

7.1 Immunosuppressive Treatments

Corticosteroids, other immunosuppressive agents or treatments, and immunosuppressive illnesses can interfere with the development of active immunity and predispose the patient to developing rabies [See Dosage and Administration (2.1, 2.2)]. Immunosuppressive agents should not be administered during post-exposure prophylaxis, unless essential for the treatment of other conditions. When rabies post-exposure prophylaxis is administered to individuals receiving steroids or other immunosuppressive therapy, it is especially important that serum be tested for an RVNA titer to ensure that an adequate response has developed. (3)

8 USE IN SPECIFIC POPULATIONS

8.1 Pregnancy

Risk Summary

All pregnancies have a risk of birth defect, loss, or other adverse outcomes. In the US general population, the estimated background risk of major birth defects and miscarriage in clinically recognized pregnancies is 2% to 4% and 15% to 20%, respectively.

There are no adequate and well-controlled studies of IMOVAX RABIES in pregnant women. Data on IMOVAX RABIES administered to pregnant women are insufficient to inform vaccine-associated risks in pregnancy.

Animal reproduction studies have not been conducted with IMOVAX RABIES.

Clinical considerations

Disease-Associated Maternal and/or Embryo/Fetal Risk

Confirmed rabies infection nearly always results in death.

8.2 Lactation

Risk Summary

It is not known whether IMOVAX RABIES is excreted in human milk. Data are not available to assess the effects of IMOVAX RABIES on the breastfed infant or on milk production/excretion.

The developmental and health benefits of breastfeeding should be considered along with the mother's clinical need for IMOVAX RABIES and any potential adverse effects on the breastfed child from IMOVAX RABIES or from the underlying maternal condition. For preventive vaccines, the underlying maternal condition is susceptibility to the disease prevented by the vaccine.

8.4 Pediatric Use

Safety and efficacy have been established in all pediatric age groups [See Adverse Reactions (6.1) and Clinical Studies (14)].

8.5 Geriatric Use

Clinical studies of IMOVAX RABIES did not include sufficient numbers of participants aged 65 and over to determine whether they respond differently from younger participants [See Adverse Reactions (6.1) and Clinical Studies (14)].

11 DESCRIPTION

IMOVAX RABIES (Rabies Vaccine) is a sterile, injectable suspension for intramuscular use. IMOVAX RABIES is supplied as a vial of lyophilized vaccine which must be reconstituted with the accompanying Sterile Water diluent. The vaccine is prepared from rabies vaccine virus strain PM-1503-3M.

The vaccine virus is harvested from infected human diploid cells, MRC-5 cell line, concentrated by ultrafiltration and is inactivated by beta-propiolactone. One dose of reconstituted vaccine contains less than 100 mg human albumin, less than 150 mcg neomycin sulfate and 20 mcg of phenol red indicator. Beta-propiolactone, a residual component of the manufacturing process, is present in less than 50 parts per million. IMOVAX RABIES contains no preservative.

The potency of one dose (1 mL) of IMOVAX RABIES is equal to or greater than 2.5 international units (IU) of rabies antigen.

The vial stopper, the plunger rod and the tip cap of the syringe are not made with natural rubber latex.

12 CLINICAL PHARMACOLOGY

12.1 Mechanism of Action

Protection after vaccination is provided by the induction of rabies virus neutralizing antibodies.

13 NONCLINICAL TOXICOLOGY

13.1 Carcinogenesis, Mutagenesis, Impairment of Fertility

IMOVAX RABIES has not been evaluated for carcinogenic or mutagenic potential or for impairment of fertility in animals.

14 CLINICAL STUDIES

14.1 Pre-exposure Prophylaxis

Three-dose regimen for pre-exposure prophylaxis

Antibody responses to IMOVAX RABIES have been demonstrated in trials conducted in England (13), Germany (14) (15), France (16) and Belgium. (17) In the US, IMOVAX RABIES resulted in geometric mean titers (GMT) of 12.9 IU/mL at Day 49 and 5.1 IU/mL at Day 90 when three doses were given intramuscularly during the course of one month. The range of RVNA responses was 2.8 to 55.0 IU/mL at Day 49 and 1.8 to 12.4 IU/mL at Day 90. (18) The definition of a minimally accepted RVNA titer varies among laboratories and is influenced by the type of test conducted. The thresholds for an adequate immune response used in these trials were either 1:5 or 0.5 IU/mL depending on the trials.

Two-dose regimen for pre-exposure prophylaxis

The two-dose regimen (on Day 0, and Day 7) was assessed in two phase 3 studies.

In one observer-blind, randomized, controlled, multicenter study conducted in Thailand (Study 2), RVNA responses after 2 doses of IMOVAX RABIES were compared to RVNA responses after 3 doses of IMOVAX RABIES. In this study, 100 healthy participants 18 years of age and older (including 2 participants 65 years of age and older), and 100 participants 1 year through 17 years of age received a 3-dose pre-exposure prophylaxis regimen of IMOVAX RABIES. A key secondary objective of the study was to demonstrate in the pooled participants (from 1 year through 17 years of age and 18 years of age and older), the noninferiority of a 2-dose pre-exposure prophylaxis regimen of IMOVAX RABIES (on Day 0, and Day 7) at Day 28 compared to the 3-dose pre-exposure prophylaxis regimen of IMOVAX RABIES (on Day 0, Day 7, and Day 28) at Day 42 in terms of the percentage of participants with an RVNA titer ≥ 0.5 IU/mL. The analysis was done in the per protocol analysis set (PPAS) with data from Day 28 and Day 42 contributed from the same participants, and with the prespecified noninferiority margins of -10% and -5%.

At Day 28 (after 2 doses of IMOVAX RABIES), 98.8% of participants had an RVNA titer ≥ 0.5 IU/mL. At Day 42 (after 3 doses of IMOVAX RABIES), 100% participants had an RVNA titer ≥ 0.5 IU/mL. The difference in the percentage of participants who achieved an RVNA titer ≥ 0.5 IU/mL was -1.3% [95% confidence interval (CI): -4.4; 1.3]. As the lower bound of the 95% CI of this difference (-4.4%) was greater than the prespecified noninferiority margins of -10% and -5%, noninferiority of the 2-dose pre-exposure prophylaxis regimen at Day 28 to the 3-dose pre-exposure prophylaxis regimen at Day 42 was demonstrated.

In an open-label, randomized, controlled, multicenter study (Study 1) conducted in the Philippines, 228 healthy participants (including 101 participants from 2 years through 17 years of age and 127 participants 18 years through 52 years of age) were randomized to receive the 2-dose pre-exposure prophylaxis regimen of IMOVAX RABIES and 115 healthy participants (including 46 participants from 2 years through 17 years of age and 69 participants 18 years through 59 years of age) were randomized to receive a 3-dose pre-exposure prophylaxis regimen of IMOVAX RABIES. One year later, 200 participants from the 2-dose pre-exposure prophylaxis group and 107 participants from the 3-dose pre-exposure prophylaxis group received two doses of IMOVAX RABIES 3 days apart (on Day 0 and Day 3) to mimic a post-exposure prophylaxis regimen without actual rabies exposure (simulated post-exposure prophylaxis).

The primary objective of the study was to demonstrate noninferiority of a 2-dose pre-exposure prophylaxis regimen of IMOVAX RABIES (on Day 0 and Day 7) at Day 21 compared with the 3-dose pre-exposure prophylaxis regimen of IMOVAX RABIES (on Day 0, Day 7 and Day 28) at Day 35, in terms of the percentage of participants with an RVNA titer ≥ 0.5 IU/mL. The analysis was done in the PPAS with the prespecified noninferiority margin of -5%.

At Day 21, 96.7% of participants who received the 2-dose pre-exposure prophylaxis regimen of IMOVAX RABIES had an RVNA titer ≥ 0.5 IU/mL. At Day 35, 100% participants who received the 3-dose pre-exposure prophylaxis regimen of IMOVAX RABIES had an RVNA titer ≥ 0.5 IU/mL. Noninferiority was not demonstrated as the difference in the percentage of participants who had an RVNA titer ≥ 0.5 IU/mL threshold was ‑3.3% (95% CI: -6.8; 0.5) and the lower bound of the 95% CI was below the prespecified noninferiority margin (‑5%). All participants 2 years through 17 years of age who received the 2-dose pre-exposure prophylaxis regimen of IMOVAX RABIES had an RVNA titer ≥ 0.5 IU/mL at Day 21.

One year later, following the simulated post-exposure prophylaxis, 100% of participants primed with either a 2-dose or 3-dose pre-exposure prophylaxis regimen of IMOVAX RABIES had an RVNA titer ≥ 0.5 IU/mL at 7 and 14 days after the first simulated post-exposure prophylaxis injection, which demonstrated an anamnestic response.

14.2 Post-exposure Prophylaxis

Post-exposure efficacy of IMOVAX RABIES was demonstrated during clinical experience in Iran in which six 1 mL doses were given on Days 0, 3, 7, 14, 30, and 90, in conjunction with antirabies serum. Forty-five individuals severely bitten by rabid dogs and wolves received IMOVAX RABIES within hours of and up to 14 days after the bites. All individuals were fully protected against rabies. (19)

Studies conducted by the CDC have shown that a regimen of 1 dose of Rabies Immune Globulin (RIG) and 5 doses of IMOVAX RABIES induced a sufficient antibody response in all recipients. Of 511 individuals bitten by proven rabid animals and so treated, none developed rabies. (7)

15 REFERENCES

1 Rao AK, Briggs D, Moore SM, et al. Use of a Modified Preexposure Prophylaxis Vaccination Schedule to Prevent Human Rabies: Recommendations of the Advisory Committee on Immunization Practices - United States, 2022. MMWR. 2022;71(18):619–627.
2 Rupprecht CE, Briggs D, Brown CM, et al. Use of a Reduced (4-Dose) Vaccine Schedule for Postexposure Prophylaxis to Prevent Human Rabies: Recommendations of the Advisory Committee on Immunization Practices. MMWR. 2010;59(RR-2):1–9.
3 Manning SE, Rupprecht CE, Fishbein D, et al. Human rabies prevention - United States, 2008: Recommendations of the Advisory Committee on Immunization Practices. MMWR. 2008;57(RR-3):1–28.
4 CDC. Human rabies despite treatment with rabies immune globulin and human diploid cell rabies vaccine - Thailand. MMWR. 1987;36(46):759–760, 765.
5 Cockshott WP, Thompson GT, Howlett LJ, et al. Intramuscular or intralipomatous injections? N Engl J Med. 1982;307(6):356–358.
6 Baer GM, Fishbein DB. Rabies postexposure prophylaxis. N Engl J Med. 1987;316:1270–1272.
7 CDC. Recommendations of the Advisory Committee on Immunization Practices. Rabies Prevention--United States, 1984. MMWR. 1984;33(28):393–402, 407–408.
8 Shill M, Baynes RD, Miller SD. Fatal rabies encephalitis despite appropriate post-exposure prophylaxis. N Engl J Med. 1987;316(20):1257–1258.
9 CDC. Systemic allergic reactions following immunization with human diploid cell rabies vaccine. MMWR. 1984;33(14):185–187.
10 Boe E, Nyland H. Guillain-Barré syndrome after vaccination with human diploid cell rabies vaccine. Scand J Infect Dis. 1980;12(3):231–232.
11 CDC. Adverse reactions to human diploid cell rabies vaccine. MMWR. 1980;29:609–610.
12 Bernard KW, Smith PW, Kader FJ, et al. Neuroparalytic illness and human diploid cell rabies vaccine. JAMA. 1982;248(23):3136–3138.
13 Aoki FY, Tyrrell DAJ, Hill LE. Immunogenicity and acceptability of a human diploid-cell culture rabies vaccine in volunteers. Lancet. 1975;1(7908):660–662.
14 Cox JH, Schneider LG. Prophylactic immunization of humans against rabies by intradermal inoculation of human diploid cell culture vaccine. J Clin Microbiol. 1976;3(2):96–101.
15 Kuwert EK, Marcus I, Werner J, et al. Some experiences with human diploid cell strain (HDCS) rabies vaccine in pre- and post-exposure vaccinated humans. Dev Biol Stand. 1978;40:79–88.
16 Ajjan N, Soulebot JP, Stellmann C, et al. Résultats de la vaccination antirabique préventive par le vaccin inactivé concentré souche rabies PM/W138-1503-3M cultivés sur cellules diploïdes humaines. [Results of preventive rabies vaccination with a concentrated vaccine of the PM/WI38-1503-3M rabies strain cultured on human diploid cells. Preparation of mixed antirabies-antitetanus hyperimmune immunoglobulin by plasmapheresis of blood taken from vaccinated veterinary students]. Dev Biol Stand. 1978;40:89–100.
17 Costy-Berger F. Vaccination antirabique préventive par du vaccin préparé sur cellules diploïdes humaines [Preventive rabies vaccination using vaccine prepared from human diploid cells]. Dev Biol Stand. 1978;40:101–104.
18 Bernard KW, Roberts MA, Sumner J, et al. Human diploid cell rabies vaccine. JAMA. 1982;247(8):1138–1142.
19 Bahmanyar M, Fayaz A, Nour-Salehi S, et al. Successful protection of humans exposed to rabies infection. JAMA. 1976;236(24):2751–2754.

16 HOW SUPPLIED/STORAGE AND HANDLING

16.1 How Supplied

IMOVAX RABIES is supplied in a box (NDC 49281-252-51) with:

- One vial containing lyophilized vaccine (NDC 49281-246-58).
- One syringe containing Sterile Water diluent (NDC 49281-263-58). If not already inserted into the syringe, a separate plunger rod is provided.
- One sterile disposable needle for reconstitution.

Reconstitute one vial of the lyophilized vaccine with Sterile Water diluent in the accompanying syringe to form IMOVAX RABIES. A single dose after reconstitution is 1 mL.

16.2 Storage and Handling

Storage before Reconstitution

Store refrigerated between 2°C and 8°C (35°F to 46°F) in the original carton.

Do not freeze.

Storage after Reconstitution

Administer IMOVAX RABIES immediately after reconstitution.

17 PATIENT COUNSELING INFORMATION

Advise the vaccine recipient or caregiver to read the FDA-approved labeling.

Inform the vaccine recipient or caregiver about:

- Potential benefits and risks with IMOVAX RABIES.
- Potential side effects that have been reported with administration of IMOVAX RABIES.
- Reporting any side effects to their healthcare provider, the vaccine manufacturer at 1-800-822-2463 (1-800-VACCINE) (or online at https://ae.reporting.sanofi), or to the Vaccine Adverse Event Reporting System (VAERS) at 1-800-822-7967 or online at https://vaers.hhs.gov.
- Requesting medical advice before taking corticosteroids or other immunosuppressive agents as they can interfere with the immune response to the vaccine.

IMOVAX is a registered trademark of Sanofi Pasteur.
Luer-Lok is a registered trademark of Becton Dickinson and Company.

© 2026 Sanofi Pasteur Inc. – All rights reserved

Manufactured by:
Sanofi Winthrop Industrie
Marcy l'Etoile France

Distributed by:
Sanofi Pasteur Inc.
Swiftwater, PA 18370 USA
1-800-VACCINE (1-800-822-2463)

PRINCIPAL DISPLAY PANEL - 1 mL Vial Label

Rabies
Vaccine
IMOVAX® RABIES

RABIES
(HDCV)

single-dose vial (1 mL)

IM only

Rx only

Mfd by: Sanofi Pasteur SA

Lyon France US Govt Lic #1724
Dist by: Sanofi Pasteur Inc.
Swiftwater PA 18370 USA
1-800-VACCINE (1-800-822-2463)

PRINCIPAL DISPLAY PANEL - 1 mL Syringe Label

Sterile Water,
diluent for
reconstitution USP

single-dose (1 mL)

Rx only

Contains no preservative

PRINCIPAL DISPLAY PANEL - Kit Carton

NDC 49281-252-51
List No 2501

RABIES
(HDCV)

Rabies Vaccine
IMOVAX® RABIES
PRE- AND POSTEXPOSURE
INTRAMUSCULAR IMMUNIZATION ONLY

Single-dose (1 mL)

NOT FOR INTRADERMAL USE

Rx only

Wistar Rabies Virus Strain PM-1503-3M-Grown in Human Diploid Cell
Cultures-Single Dose-Lyophilized Vaccine, Luer Syringe with Sterile water,
diluent for reconstitution
USP, one needle for reconstitution.

FOR INTRAMUSCULAR INJECTION

sanofi